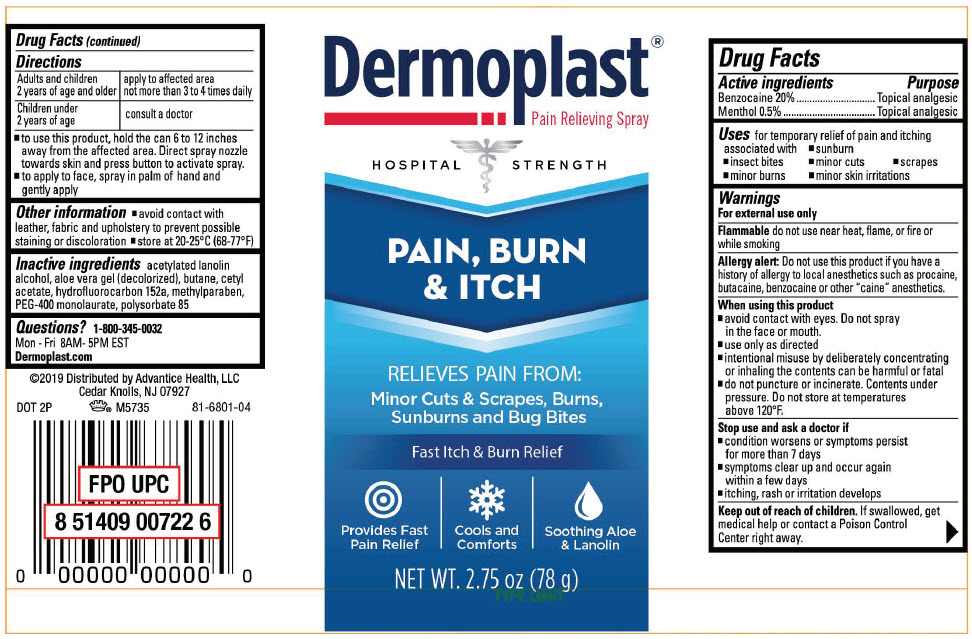 DRUG LABEL: Dermoplast Pain Relieving
NDC: 16864-680 | Form: SPRAY
Manufacturer: Advantice Health, LLC
Category: otc | Type: HUMAN OTC DRUG LABEL
Date: 20241212

ACTIVE INGREDIENTS: BENZOCAINE 200 mg/1 g; LEVOMENTHOL 5 mg/1 g
INACTIVE INGREDIENTS: PEG-8 LAURATE; POLYSORBATE 85; METHYLPARABEN; ALOE VERA LEAF; ACETYLATED LANOLIN ALCOHOLS; CETYL ACETATE; BUTANE; 1,1-DIFLUOROETHANE

Dermoplast®Pain Relieving

Drug Facts

ACTIVE INGREDIENT

Active ingredients | Purpose
Benzocaine 20% | Topical analgesic
Menthol 0.5% | Topical analgesic

Uses

for temporary relief of pain and itching associated with

- sunburn
- insect bites
- minor cuts
- scrapes
- minor burns
- minor skin irritations

Warnings

For external use only

Flammabledo not use near heat, flame, or fire or while smoking

Allergy alert

Do not use this product if you have a history of allergy to local anesthetics such as procaine, butacaine, benzocaine or other "caine" anesthetics.

When using this product

- avoid contact with eyes. Do not spray in the face or mouth.
- use only as directed
- intentional misuse by deliberately concentrating or inhaling the contents can be harmful or fatal
- do not puncture or incinerate. Contents under pressure. Do not store at temperatures above 120°F.

Stop use and ask a doctor if

- condition worsens or symptoms persist for more than 7 days
- symptoms clear up and occur again within a few days
- itching, rash or irritation develops

Keep out of reach of children.If swallowed, get medical help or contact a Poison Control Center right away.

Directions

Adults and children 2 years of age and older | apply to affected area not more than 3 to 4 times daily
Children under 2 years of age | consult a doctor

- to use this product, hold the can 6 to 12 inches away from the affected area. Direct spray nozzle towards skin and press button to activate spray.
- to apply to face, spray in palm of hand and gently apply

Other information

- avoid contact with leather, fabric and upholstery to prevent possible staining or discoloration
- store at 20-25°C (68-77°F)

Inactive ingredients

acetylated lanolin alcohol, aloe vera gel (decolorized), butane, cetyl acetate, hydrofluorocarbon 152a, methylparaben, PEG-400 monolaurate, polysorbate 85

Questions?

1-800-345-0032
Mon - Fri 8AM- 5PM EST
Dermoplast.com

Distributed by Advantice Health, LLC
Cedar Knolls, NJ 07927

PRINCIPAL DISPLAY PANEL - 78 g Can Label

Dermoplast®
Pain Relieving Spray

HOSPITAL STRENGTH

PAIN, BURN
& ITCH

RELIEVES PAIN FROM:
Minor Cuts & Scrapes, Burns,
Sunburns and Bug Bites

Fast Itch & Burn Relief

Provides Fast
Pain Relief

Cools and
Comforts

Soothing Aloe
& Lanolin

NET WT. 2.75 oz (78 g)